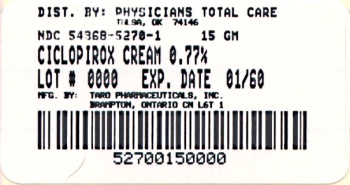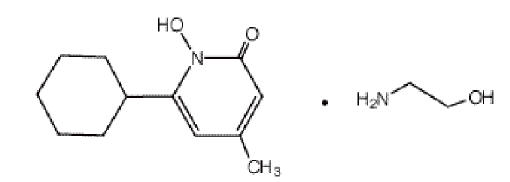 DRUG LABEL: Ciclopirox Olamine
NDC: 54868-5270 | Form: CREAM
Manufacturer: Physicians Total Care, Inc.
Category: prescription | Type: HUMAN PRESCRIPTION DRUG LABEL
Date: 20130219

ACTIVE INGREDIENTS: ciclopirox olamine 7.7 mg/1 g
INACTIVE INGREDIENTS: benzyl alcohol; cetyl alcohol; Coco Diethanolamide; lactic acid; mineral oil; myristyl alcohol; octyldodecanol; polysorbate 60; water; sorbitan monostearate; stearyl alcohol

Ciclopirox Olamine
Cream USP, 0.77%

Rx Only

FOR DERMATOLOGIC USE ONLY
NOT FOR OPHTHALMIC USE

DESCRIPTION

Ciclopirox Olamine Cream USP, 0.77% is for topical use.

Each gram of Ciclopirox Olamine Cream USP contains 7.70 mg of ciclopirox (as ciclopirox olamine) in a water miscible vanishing cream base consisting of cetyl alcohol, cocamide DEA, lactic acid, mineral oil, myristyl alcohol, octyldodecanol, polysorbate 60, purified water, sorbitan monostearate, stearyl alcohol, and benzyl alcohol (1%) as preservative.

Ciclopirox olamine cream contains a synthetic, broad-spectrum, antifungal agent ciclopirox (as ciclopirox olamine). The chemical name is 6-cyclohexyl-1-hydroxy-4-methyl-2(1H)-pyridone, 2-aminoethanol salt.

The CAS Registry Number is 41621-49-2. The chemical structure is:

Ciclopirox olamine cream has a pH of 7.

CLINICAL PHARMACOLOGY

Ciclopirox is a broad-spectrum, antifungal agent that inhibits the growth of pathogenic dermatophytes, yeasts, and Malassezia furfur. Ciclopirox exhibits fungicidal activity in vitro against isolates of Trichophyton rubrum, Trichophyton mentagrophytes, Epidermorphyton floccosum, Microsporum canis, and Candida albicans.

Pharmacokinetic studies in men with tagged ciclopirox solution in polyethylene glycol 400 showed an average of 1.3% absorption of the dose when it was applied topically to 750 cm^2 on the back followed by occlusion for 6 hours. The biological half-life was 1.7 hours and excretion occurred via the kidney. Two days after application only 0.01% of the dose applied could be found in the urine. Fecal excretion was negligible.

Penetration studies in human cadaverous skin from the back, with Ciclopirox Olamine Cream USP, 0.77% with tagged ciclopirox showed the presence of 0.8 to 1.6% of the dose in the stratum corneum 1.5 to 6 hours after application. The levels in the dermis were still 10 to 15 times above the minimum inhibitory concentrations.

Autoradiographic studies with human cadaverous skin showed that ciclopirox penetrates into the hair and through the epidermis and hair follicles into the sebaceous glands and dermis, while a portion of the drug remains in the stratum corneum.

Draize Human Sensitization Assay, 21-Day Cumulative Irritancy study, Phototoxicity study, and Photo-Draize study conducted in a total of 142 healthy male subjects showed no contact sensitization of the delayed hypersensitivity type, no irritation, no phototoxicity, and no photo-contact sensitization due to Ciclopirox Olamine Cream USP, 0.77%.

INDICATIONS AND USAGE

Ciclopirox olamine cream is indicated for the topical treatment of the following dermal infections: tinea pedis, tinea cruris, and tinea corporis due to Trichophyton rubrum, Trichophyton mentagrophytes, Epidermophyton floccosum, and Microsporum canis; candidiasis (moniliasis) due to Candida albicans; and tinea (pityriasis) versicolor due to Malassezia furfur.

CONTRAINDICATIONS

Ciclopirox olamine cream is contraindicated in individuals who have shown hypersensitivity to any of its components.

WARNINGS

Ciclopirox olamine cream is not for ophthalmic use.

Keep out of reach of children.

PRECAUTIONS

If a reaction suggesting sensitivity or chemical irritation should occur with the use of ciclopirox olamine cream, treatment should be discontinued and appropriate therapy instituted.

Information for Patients

The patient should be told to:

1. Use the medication for the full treatment time even though symptoms may have improved and notify the physician if there is no improvement after four weeks.
2. Inform the physician if the area of application shows signs of increased irritation (redness, itching, burning, blistering, swelling, or oozing) indicative of possible sensitization.
3. Avoid the use of occlusive wrappings or dressings.

Carcinogenesis, Mutagenesis, Impairment of Fertility

A carcinogenicity study in female mice dosed cutaneously twice per week for 50 weeks followed by a 6-month drug-free observation period prior to necropsy revealed no evidence of tumors at the application site.

The following in vitro and in vivo genotoxicity tests have been conducted with ciclopirox olamine: studies to evaluate gene mutation in the Ames Salmonella/Mammalian Microsome Assay (negative) and Yeast Saccharomyces Cerevisiae Assay (negative) and studies to evaluate chromosome aberrations in vivo in the Mouse Dominant Lethal Assay and in the Mouse Micronucleus Assay at 500 mg/kg (negative).

The following battery of in vitro genotoxicity tests were conducted with ciclopirox: a chromosome aberration assay in V79 Chinese Hamster Cells, with and without metabolic activation (positive); a gene mutation assay in the HGPRT – test with V79 Chinese Hamster Cells (negative); and a primary DNA damage assay (i.e., unscheduled DNA Synthesis Assay in A549 Human Cells (negative)). An in vitro Cell Transformation Assay in BALB/C3T3 Cells was negative for cell transformation. In an in vivo Chinese Hamster Bone Marrow Cyctogenetic Assay, ciclopirox was negative for chromosome aberrations at 5000 mg/kg.

Pregnancy Category B

Reproduction studies have been performed in the mouse, rat, rabbit, and monkey (via various routes of administration) at doses 10 times or more the topical human dose and have revealed no significant evidence of impaired fertility or harm to the fetus due to ciclopirox. There are, however, no adequate or well-controlled studies in pregnant women. Because animal reproduction studies are not always predictive of human response, this drug should be used during pregnancy only if clearly needed.

Nursing Mothers

It is not known whether this drug is excreted in human milk. Because many drugs are excreted in human milk, caution should be exercised when Ciclopirox Olamine Cream USP, 0.77% is administered to a nursing woman.

Pediatric Use

Safety and effectiveness in pediatric patients below the age of 10 years have not been established.

ADVERSE REACTIONS

In all controlled clinical studies with 514 patients using ciclopirox olamine cream and in 296 patients using the vehicle cream, the incidence of adverse reactions was low. This included pruritus at the site of application in one patient and worsening of the clinical signs and symptoms in another patient using ciclopirox cream and burning in one patient and worsening of the clinical signs and symptoms in another patient using the vehicle cream.

DOSAGE AND ADMINISTRATION

Gently massage Ciclopirox Olamine Cream USP, 0.77% into the affected and surrounding skin areas twice daily, in the morning and evening. Clinical improvement with relief of pruritus and other symptoms usually occurs within the first week of treatment. If a patient shows no clinical improvement after four weeks of treatment with ciclopirox olamine cream, the diagnosis should be redetermined. Patients with tinea versicolor usually exhibit clinical and mycological clearing after two weeks of treatment.

HOW SUPPLIED

Ciclopirox Olamine Cream USP, 0.77% is supplied in tubes of:

15 g (NDC 54868-5270-1)

30 g (NDC 54868-5270-2)

90 g (NDC 54868-5270-0)

STORAGE AND HANDLING

Store at 20°-25°C (68°-77°F) [see USP Controlled Room Temperature].

Mfd. by: Taro Pharmaceuticals Inc., Brampton, Ontario, Canada L6T 1C1
Dist. by: Taro Pharmaceuticals U.S.A., Inc., Hawthorne, NY 10532

Issued: March 2005

PK-4597-0 125

Additional bar code labeling by:
Physicians Total Care, Inc.
Tulsa, Oklahoma 74146

PRINCIPAL DISPLAY PANEL

Ciclopirox Olamine
Cream USP, 0.77%

FOR DERMATOLOGIC USE ONLY.
NOT FOR OPHTHALMIC USE.

Rx only

Keep this and all medications out of the reach of children.